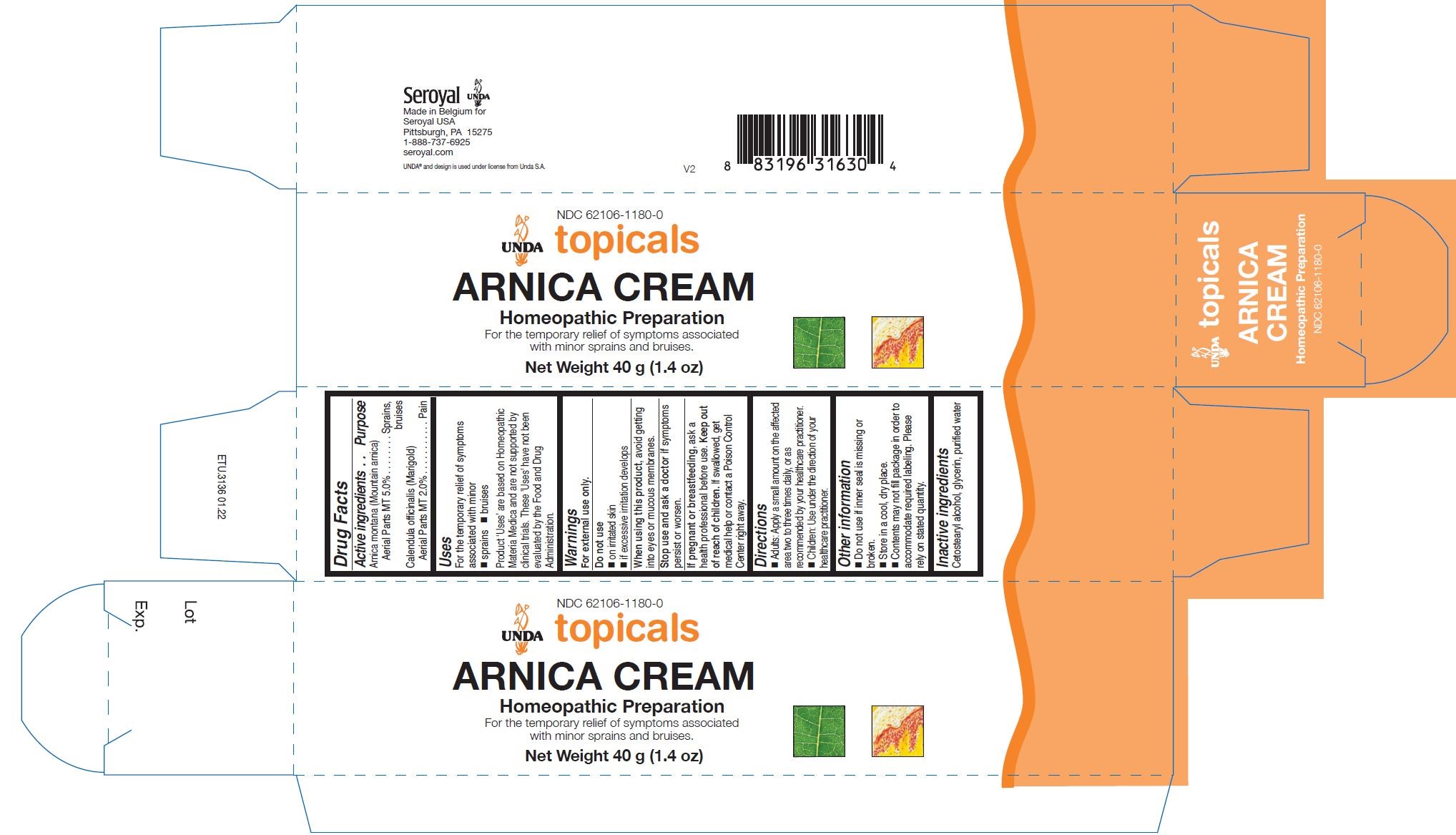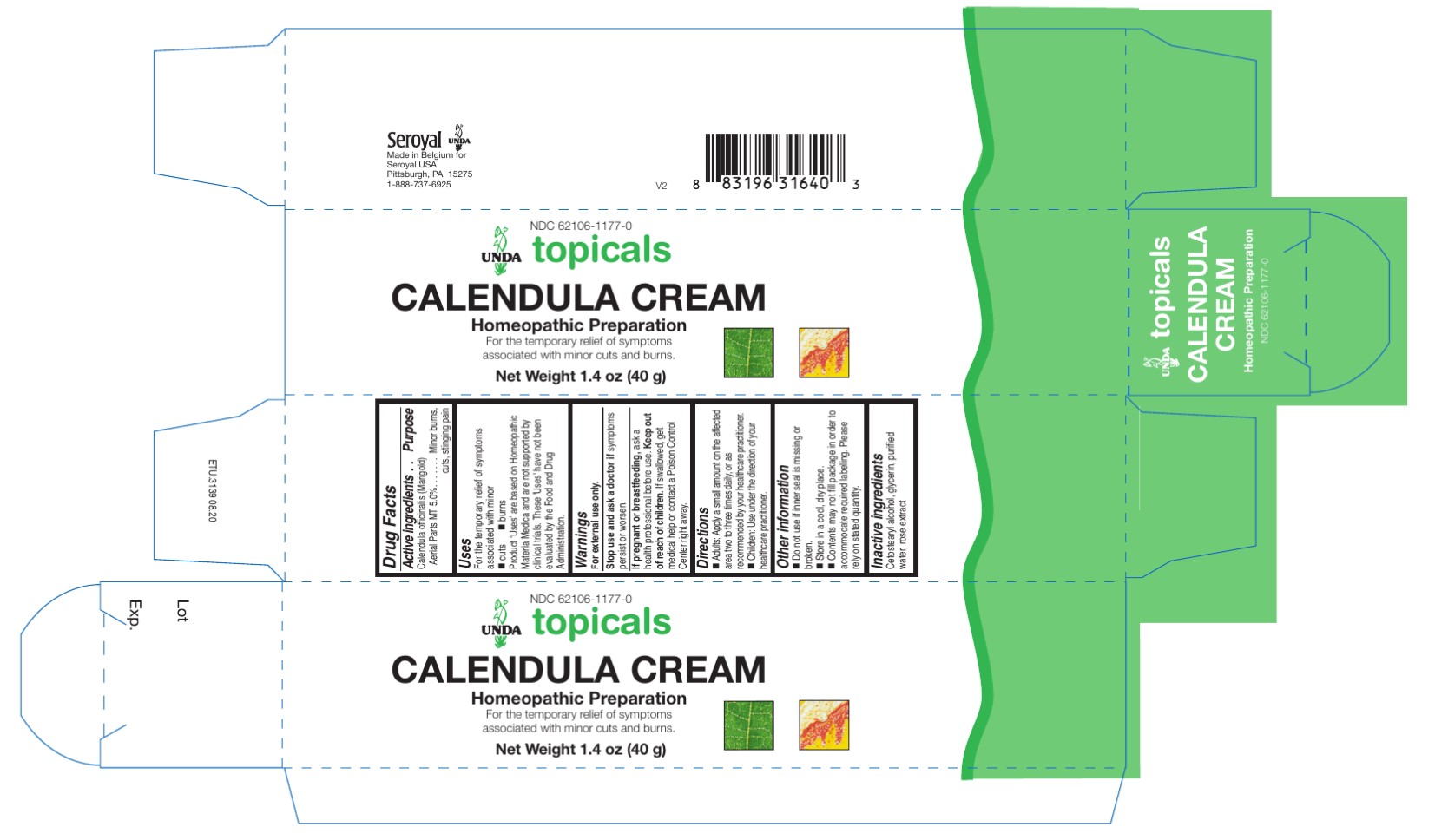 DRUG LABEL: Calendula Cream
NDC: 62106-1177 | Form: CREAM
Manufacturer: Seroyal USA
Category: homeopathic | Type: HUMAN OTC DRUG LABEL
Date: 20220412

ACTIVE INGREDIENTS: CALENDULA OFFICINALIS FLOWERING TOP 1 [hp_X]/40 g
INACTIVE INGREDIENTS: GLYCERIN; CETOSTEARYL ALCOHOL; WATER; ROSE OIL

Unda Creams

Active ingredients
Calendula officinalis (Marigold) Aerial Parts MT 5.0%

Uses
For the temporary relief of symptoms associated with minor cuts and burns

Warnings
For external use only.
Stop use and ask a doctor if symptoms persist or worsen.
If pregnant or breastfeeding, ask a health professional before use. Keep out
of reach of children. If swallowed, get medical help or contact a Poison Control
Center right away.

Keep out of reach of children.

OVERDOSAGE

If swallowed, get medical help or contact a Poison
Control Center right away.

Inactive ingredients
Cetostearyl alcohol, glycerin, purified water, rose oil

Other information
Do not use if inner seal is missing or broken.
Store in a cool, dry place.

Contents may not fill package in order to
accommodate required labeling. Please
rely on stated quantity

Directions
Adults: Apply a small amount on the affected area two to three times daily, or as
recommended by your healthcare practitioner.
Children: Use under the direction of your healthcare practitioner.

Uses
For the temporary relief of symptoms associated with minor cuts and burns

Directions
Adults: Apply a small amount on the affected area two to three times daily, or as
recommended by your healthcare practitioner.
Children: Use under the direction of your healthcare practitioner.

Active ingredients
This preparation contains:
Arnica montana (Mountain arnica)
Aerial Parts MT 5.0%
Calendula officinalis (Marigold)
Aerial Parts MT 2.0%

Uses
For the temporary relief of symptoms associated with

minor sprains and bruises.

Warnings
For external use only.
Do not use
on irritated skin
if excessive irritation develops
When using this product, avoid getting
into eyes or mucous membranes.
Stop use and ask a doctor if symptoms
persist or worsen.
If pregnant or breastfeeding, ask a
health professional before use. Keep out
of reach of children. If swallowed, get
medical help or contact a Poison Control
Center right away.

Keep out of reach of children.

OVERDOSAGE

If swallowed, get medical help or contact a Poison
Control Center right away.

Inactive ingredients
Cetostearyl alcohol, glycerin, purified water

Other information
Do not use if inner seal is missing or
broken.
Store in a cool, dry place.

Directions
Adults: Apply a small amount on the affected
area two to three times daily, or as
recommended by your healthcare practitioner.
Children: Use under the direction of your
healthcare practitioner.

Uses
For the temporary relief of symptoms associated with minor sprains and bruises.

Directions
Adults: Apply a small amount on the affected
area two to three times daily, or as
recommended by your healthcare practitioner.
Children: Use under the direction of your
healthcare practitioner.

PACKAGE LABEL

NDC 62106-1177-0

UNDA topicals

CALENDULA CREAM

Homeopathic Preparation

For the temporary relief of symptoms
associated with minor cuts and burns.

Net Weight 1.4 oz (40 g)

PACKAGE LABEL

NDC 62106-1180-0

UNDA topicals

ARNICA CREAM

Homeopathic Preparation

For the temporary relief of symptoms associated
with minor sprains and bruises.

Net Weight 1.4 oz. (40 g)